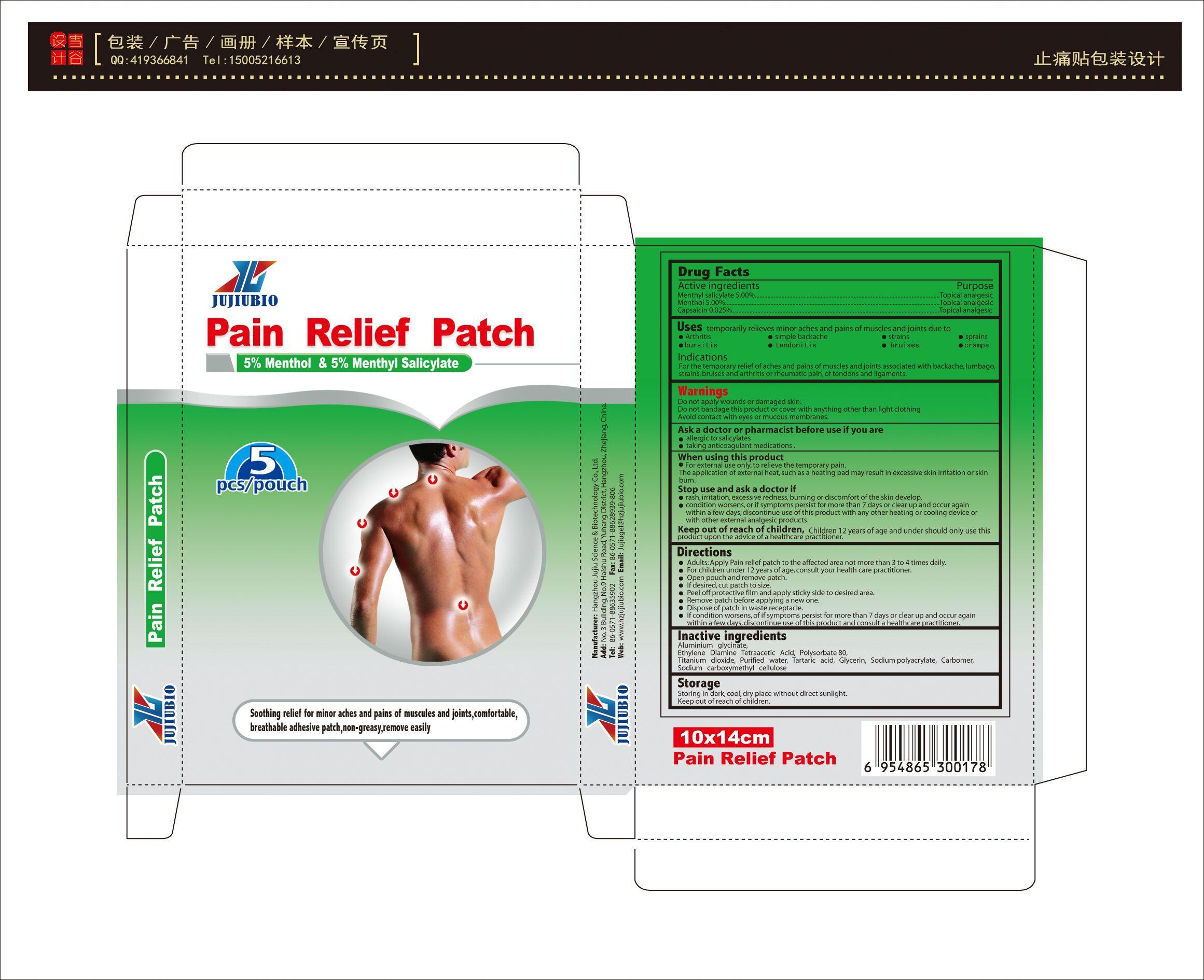 DRUG LABEL: pain relief patch
NDC: 69963-001 | Form: PATCH
Manufacturer: Hangzhou Jujiu Science & Biotechnology Co.,Ltd.
Category: otc | Type: HUMAN OTC DRUG LABEL
Date: 20180106

ACTIVE INGREDIENTS: MENTHOL 5 g/100 g; MENTHYL SALICYLATE, (+/-)- 5 g/100 g; CAPSAICIN 0.025 g/100 g
INACTIVE INGREDIENTS: ALUMINIUM TRIGLYCINATE 0.025 g/100 g; DIAMINOHYDROXYPROPANETETRAACETIC ACID 0.025 g/100 g; POLYSORBATE 80 0.025 g/100 g; TITANIUM DIOXIDE 0.025 g/100 g; WATER 0.025 g/100 g; TARTARIC ACID 0.025 g/100 g; GLYCERIN 0.025 g/100 g; SODIUM POLYACRYLATE (8000 MW) 0.025 g/100 g; CARBOMER 940 0.025 g/100 g; CARBOXYMETHYLCELLULOSE SODIUM 0.025 g/100 g

cold& hot patch

Active Ingredient

Menthyl salicylate 5.00%
Menthol 5.00%
Capsaicin 0.025%

Purpose

Topical analgesic

Use

 Arthritis
 simple backache
 strains
 sprains
 bursitis
 tendonitis
 bruises
 cramps

Warnning

Do not apply wounds or damaged skin.
Do not bandage this product or cover with anything other than light clothing
Avoid contact with eyes or mucous membranes.
Ask a doctor or pharmacist before use if you are
 allergic to salicylates
 taking anticoagulant medications .
When using this product
 For external use only, to relieve the temporary pain.
The application of external heat, such as a heating pad may result in excessive skin irritation or skin burn.
Stop use and ask a doctor if
 rash, irritation, excessive redness, burning or discomfort of the skin develop.
 condition worsens, or if symptoms persist for more than 7 days or clear up and occur again within a few days, discontinue use of this product with any other heating or cooling device or with other external analgesic products.

Keep out of reach of children, Children 12 years of age and under should only use this product upon the advice of a healthcare practitioner.

Directions

 Adults: Apply Pain relief patch to the affected area not more than 3 to 4 times daily.
 For children under 12 years of age, consult your health care practitioner.
 Open pouch and remove patch.
 If desired, cut patch to size.
 Peel off protective film and apply sticky side to desired area.
 Remove patch before applying a new one.
 Dispose of patch in waste receptacle.
 If condition worsens, of if symptoms persist for more than 7 days or clear up and occur again within a few days, discontinue use of this product and consult a healthcare practitioner.

Inactive Ingredients

Aluminium glycinate, Ethylene Diamine Tetraacetic Acid, Polysorbate 80, Titanium dioxide, Purified water, Tartaric acid, Glycerin, Sodium polyacrylate, Carbomer, Sodium carboxymethyl cellulose